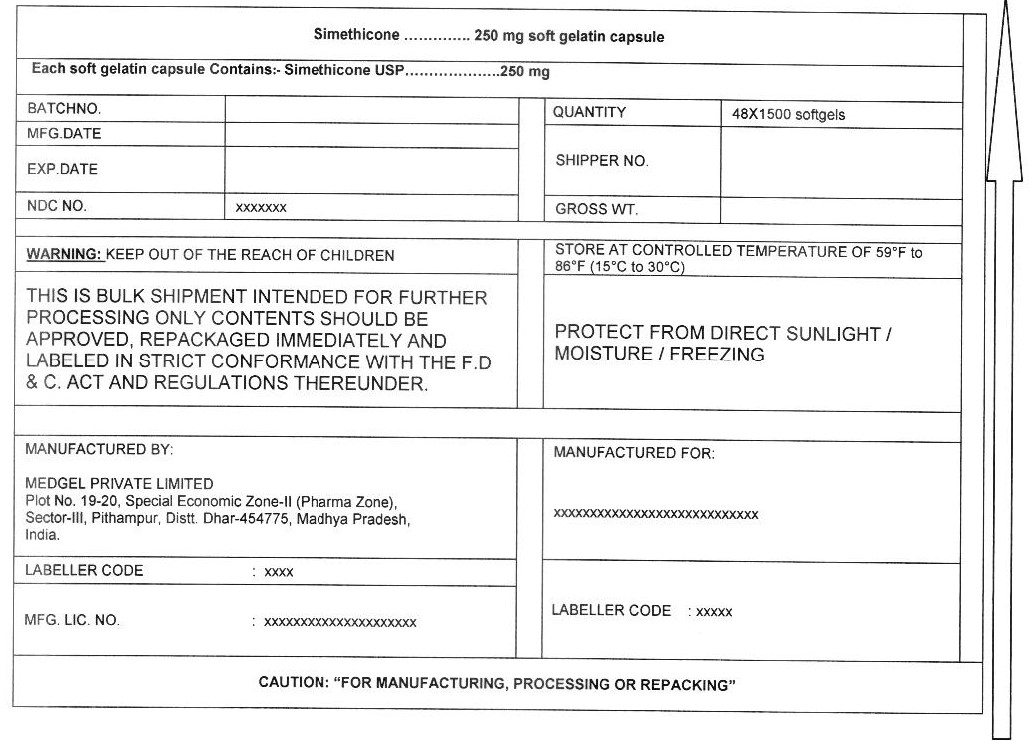 DRUG LABEL: Simethicone
NDC: 55629-017 | Form: CAPSULE, LIQUID FILLED
Manufacturer: ONE2ZEE LIMITED LIABILITY COMPANY
Category: otc | Type: HUMAN OTC DRUG LABEL
Date: 20230325

ACTIVE INGREDIENTS: DIMETHICONE 250 mg/1 1
INACTIVE INGREDIENTS: GELATIN; GLYCERIN; SORBITOL; FD&C BLUE NO. 1; D&C RED NO. 33; Povidone K30; TITANIUM DIOXIDE; WATER

SIMETHICONE CAPSULES 250 mg, liquid filled

Active ingredient (in each capsule)

Simethicone 250 mg

Purpose

Anti-gas

Uses

- relieves bloating, pressure or fullness commonly referred to as gas

Warnings

Stop use and ask a doctor if

condition persists

Keep out of reach of children.

Directions

- swallow one or two softgels after a meal
- do not exceed two softgels per 24 hours except under the advice and supervision of a physician

Other Information

- store at room temperature 59°-86°F (15°-30°C

Inactive ingredients

gelatin, glycerin, sorbitol, fd&c blue no. 1, fd&c red no. 40, povidone k30, titanium dioxide, water

PRINCIPAL DISPLAY PANEL - Shipping Label

Simethicone capsules

Each Softgel Contains:
(Simethicone 250mg)

LOT NO:
DRUM NO:
MFG DATE:
QUANTITY:
NDC NO: 55629-017-
EXP DATE:

WARNING:
KEEP OUT OF REACH OF CHILDREN

STORE CONTROLLED ROOM TEMPERATURE OF 59° - 86°F (15° - 30°C)
PROTECT FROM LIGHT, MOISTURE AND FREEZING

THIS IS A BULK SHIPMENT INTENDED FOR FURTHER PROCESSING ONLY.

CONTENTS SHOULD BE APPROVED, REPACKAGED IMMEDIATELY AND LABELED IN STRICT CONFORMANCE WITH
THE F.D & C.ACT AND REGULATIONS THEREUNDER.